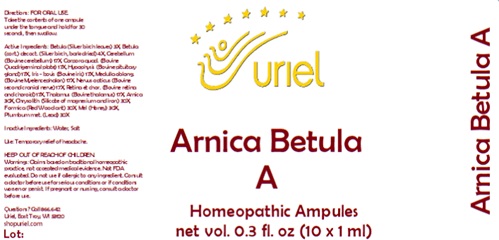 DRUG LABEL: Arnica Betula A
NDC: 48951-1352 | Form: LIQUID
Manufacturer: Uriel Pharmacy Inc.
Category: homeopathic | Type: HUMAN OTC DRUG LABEL
Date: 20231114

ACTIVE INGREDIENTS: BETULA PENDULA LEAF 3 [hp_X]/1 mL; BOS TAURUS NERVE 17 [hp_X]/1 mL; ARNICA MONTANA FLOWER 30 [hp_X]/1 mL; SILICON DIOXIDE 30 [hp_X]/1 mL; HONEY 30 [hp_X]/1 mL; FORMICA RUFA 30 [hp_X]/1 mL; LEAD 30 [hp_X]/1 mL; BOS TAURUS CEREBELLUM 17 [hp_X]/1 mL; BOS TAURUS PITUITARY GLAND 17 [hp_X]/1 mL; C12-17 ALKANE 17 [hp_X]/1 mL; BOS TAURUS EYE 17 [hp_X]/1 mL; SUS SCROFA THALAMUS 17 [hp_X]/1 mL; BETULA PUBESCENS BARK 4 [hp_X]/1 mL; BOS TAURUS BRAIN 17 [hp_X]/1 mL
INACTIVE INGREDIENTS: WATER; SODIUM CHLORIDE

Arnica Betula A

INDICATIONS AND USAGE

Directions: FOR ORAL USE.

DOSAGE AND ADMINISTRATION

Take the contents of one ampule under the tongue and hold for 30 seconds, then swallow.

ACTIVE INGREDIENT

Active Ingredients: Betula (Silver birch leaves) 3X,Betula (cort.) decoct. (Silver birch, bark dried) 4X,Cerebellum (Bovine cerebellum) 17X,Corpora quad. (Bovine Quadrigeminal plate) 17X,Hypophysis (Bovine pituitary gland) 17X,Iris - bovis (Bovine iris) 17X,Medulla oblong. (Bovine Myelencephalon) 17X,Nervus opticus (Bovine second cranial nerve) 17X,Retina et chor. (Bovine retina and choroid) 17X,Thalamus (Bovine thalamus) 17X,Arnica 30X,Chrysolith (Silicate of magnesium and iron) 30X,Formica (Red ant) 30X,Mel (Honey) 30X,Plumbum met.(Lead) 30X

Inactive Ingredients: Water, Salt

PURPOSE

Use: Temporary relief of headache.

KEEP OUT OF REACH OF CHILDREN.

WARNINGS

Warnings: Claims based on traditional homeopathic practice, not accepted medical evidence. Not FDA evaluated. Do not use if allergic to any ingredient. Consult a doctor before use for serious conditions or if conditions worsen or persist. If pregnant or nursing, consult a doctor before use.

Questions? Call 866.642.2858
Uriel, East Troy, WI 53120
shopuriel.com Lot: